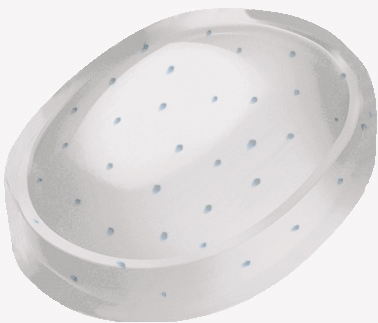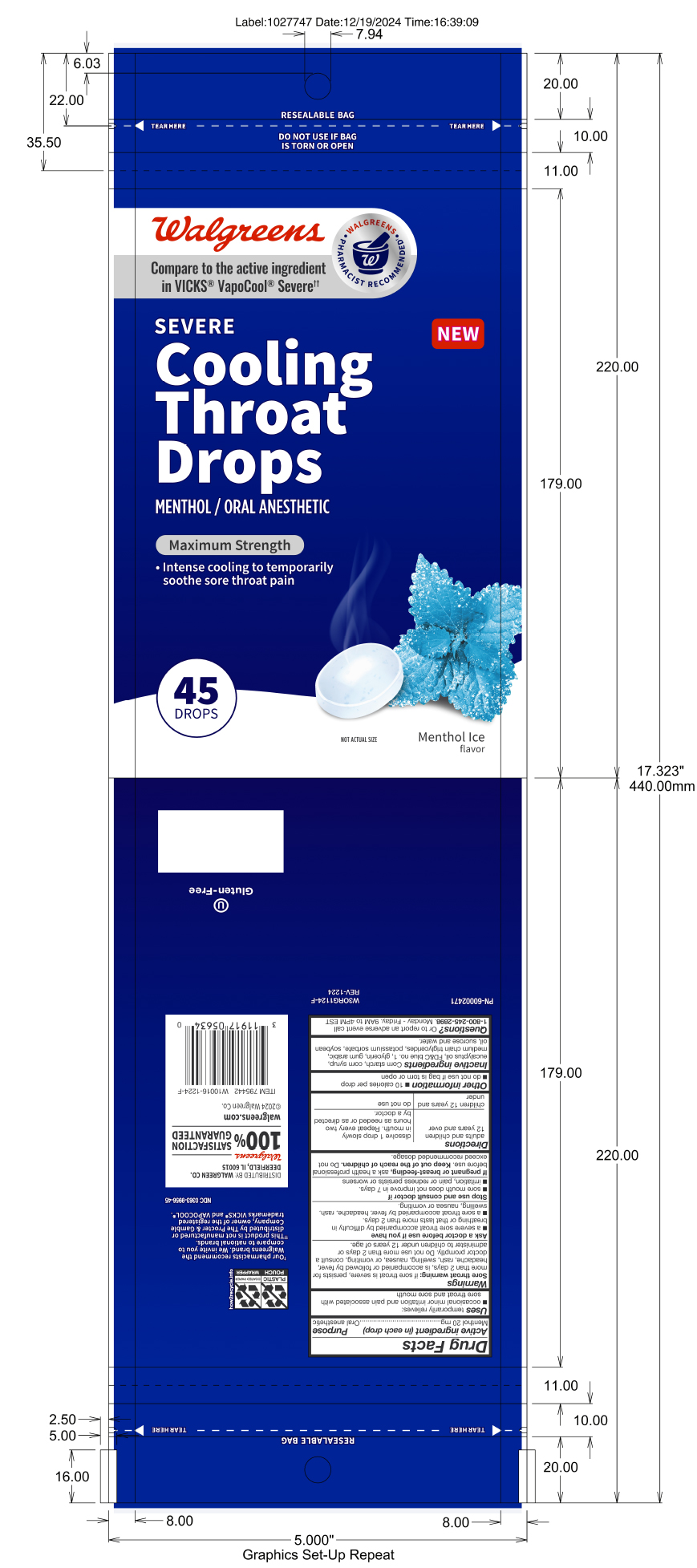 DRUG LABEL: Walgreens Severe Menthol Throat Drops
NDC: 0363-9956 | Form: LOZENGE
Manufacturer: Walgreens
Category: otc | Type: HUMAN OTC DRUG LABEL
Date: 20251223

ACTIVE INGREDIENTS: MENTHOL 20 mg/1 1
INACTIVE INGREDIENTS: WATER

Menthol 20 mg

Active ingredient (in each drop)

Menthol 20 mg

Purpose

Oral anesthetic

INDICATIONS AND USAGE

Uses temporarily relieves:

- occasional minor irritation and pain associated with sore throat and sore mouth

Warnings

Sore throat warning: if sore throat is severe, persists for more than 2 days, is accompanied or followed by fever, headache, rash, swelling, nausea, or vomiting, consult a doctor promptly. Do not use more than 2 days or administer to children under 12 years of age.

Ask a doctor before use if you have

- a severe sore throat accompanied by difficulty in breathing or that lasts more than 2 days.
- a sore throat accompanied by fever, headache, rash, swelling, nausea or vomiting.

Stop use and consult doctor if

- sore mouth does not improve in 7 days.
- irritation, pain or redness persists or worsens

PREGNANCY OR BREAST FEEDING

If pregnant or breast-feeding, ask a health professional before use.

Keep out of reach of children.

WHEN USING

Do not exceed recommended dosage.

Directions

adults and children 12 years and over dissolve 1 drop slowly in mouth. Repeat every two hours as needed or as directed by a doctor.

children 12 years and under do not use

Other information

- 10 calories per drop
- do not use if bag is torn or open

INACTIVE INGREDIENT

Inactive ingredients: Corn starch, corn syrup, eucalyptus oil, FD&C blue no. 1, glycerin, gum arabic, medium chain triglycerides, potassium sorbate, soybean oil, sucrose and water.

QUESTIONS

Questions? Or to report an adverse event call 1-800-245-2898. Monday - Friday, 9AM to 4PM EST